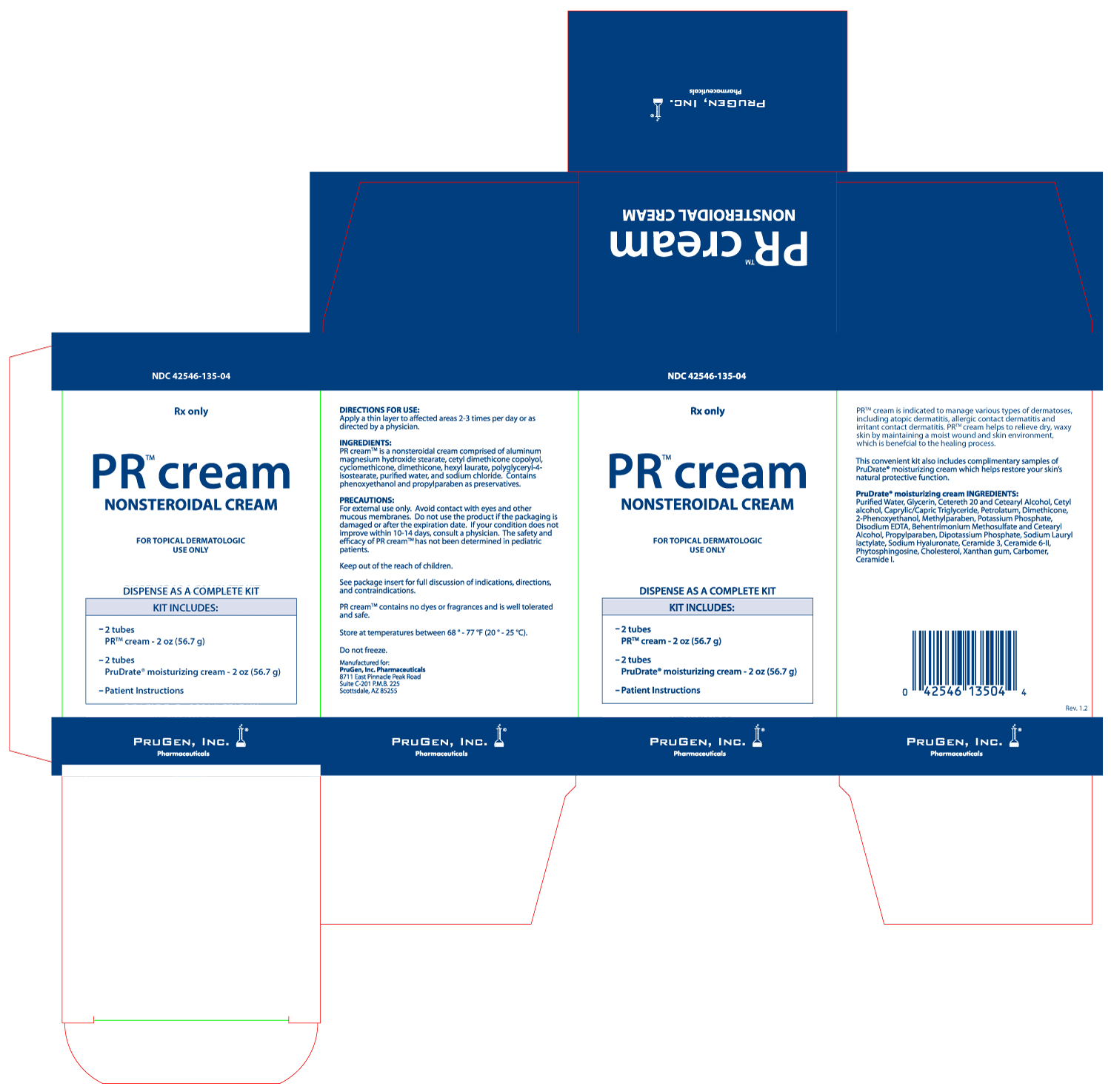 DRUG LABEL: PR Cream
NDC: 42546-135
Manufacturer: PruGen, Inc.
Category: other | Type: PRESCRIPTION MEDICAL DEVICE LABEL
Date: 20120904

PR Cream Nonsteroidal Cream

PRODUCT DESCRIPTION

PR cream is a non-sterile cream formulation intended for prescription use only.

INDICATIONS & USAGE

PR cream is indicated to manage various types of dermatoses, including atopic dermatitis, allergic contact dermatitis and irritant contact dermatitis. PR cream helps to relieve dry, waxy skin by maintaining a moist wound and skin environment, which is benefcial to the healing process.

DIRECTIONS FOR USE:

Apply a thin layer to affected areas 2-3 times per day or as directed by a physician.

INGREDIENTS

PR cream is a nonsteroidal cream comprised of aluminum magnesium hydroxide stearate, cetyl dimethicone copolyol, cyclomethicone, dimethicone, hexyl laurate, polyglyceryl-4-isostearate, purified water, and sodium chloride. Contains phenoxyethanol and propylparaben as preservatives.

CONTRAINDICATIONS

PR cream is contraindicated in persons with a known hypersensitivity to any of the components of the formulation.

PRECAUTIONS

For external use only. Avoid contact with eyes and other mucous membranes. Do not use the product if the packaging is damaged or after the expiration date. If your condition does not improve within 10-14 days, consult a physician. The safety and efficacy of PR cream has not been determined in pediatric patients.

Keep out of the reach of children.

PR cream contains no dyes or fragrances and is well tolerated and safe.

HOW SUPPLIED

PR cream is available in a kit (NDC 42546-135-04) including two net wt. 2oz. (56.7g) tubes (NDC 42546-135-02) with two complimentary net wt. 2 oz. (56.7g) tubes of PruDrate® moisturizing cream.

Store at temperatures between 68° - 77°F (20° - 25°C). Do not freeze.

Manufactured for:

PruGen, Inc. Pharmaceuticals

8711 East Pinnacle Peak Road Suite C-201 P.M.B 225

Scottsdale, AZ 85255

PR Cream Box Label

NDC 42546-135-04

PR cream Nonsteroidal Cream

For Topical Dermatological Use Only

Dispense as a complete kit

Kit includes:

-2 tubes PR cream - 2oz. (56.7g)

-2 tubes PruDrate moisturizing cream - 2oz. (56.7g)

- Patient Instructions

Rx Only

PruGen, Inc. Pharmaceuticals